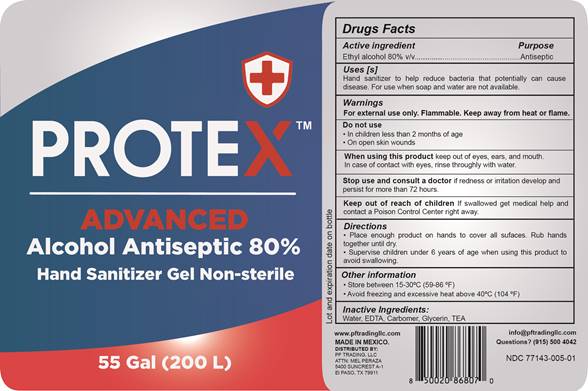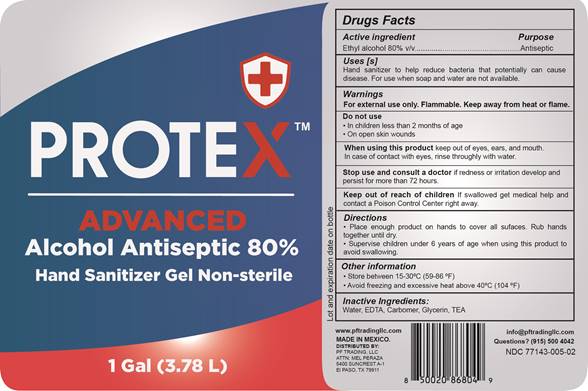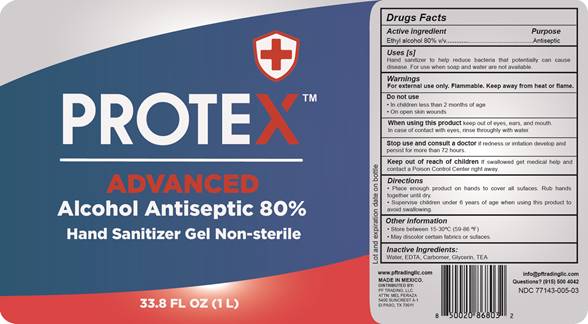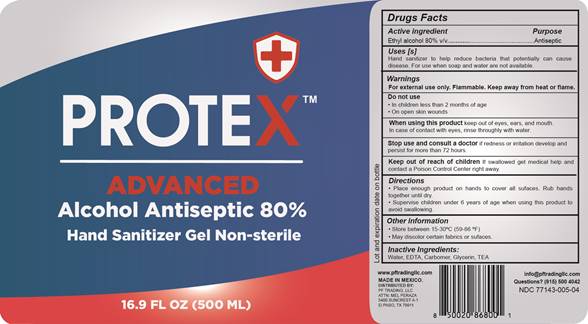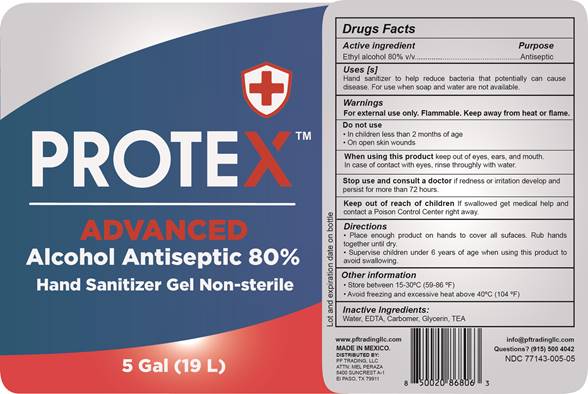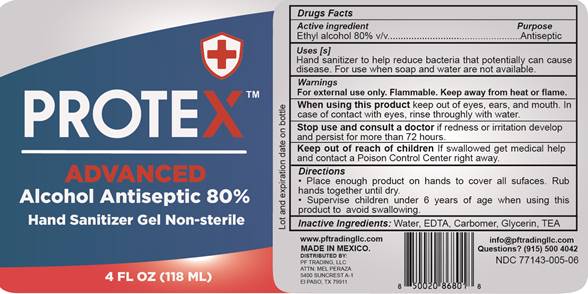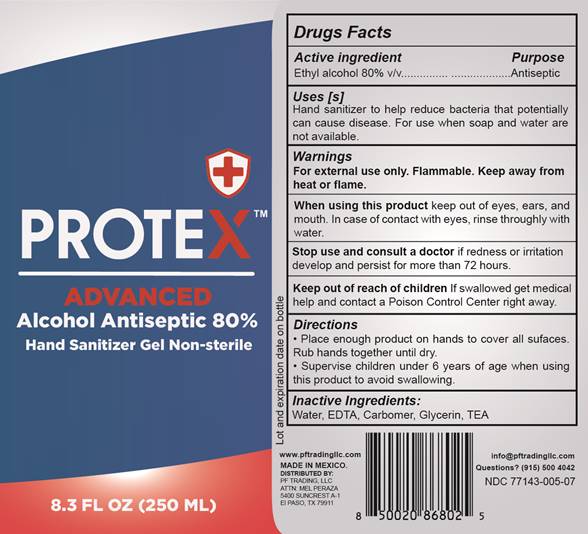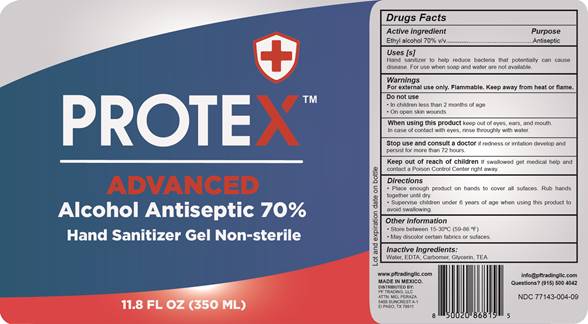 DRUG LABEL: Hand Sanitizer
NDC: 77143-005 | Form: GEL
Manufacturer: NATURATLALI S DE RL DE CV
Category: otc | Type: HUMAN OTC DRUG LABEL
Date: 20201123

ACTIVE INGREDIENTS: ALCOHOL 80 mL/100 mL
INACTIVE INGREDIENTS: GLYCERIN 0.5 mL/100 mL; CARBOMER 940 0.8 g/100 mL; WATER; TROLAMINE 0.5 g/100 mL; EDETIC ACID 0.5 mL/100 mL

ProteX NDC: 77143-005
Antibacterial 80% Alcohol

Active Ingredient(s)

Alcohol 80% v/v. Purpose: Antiseptic

Purpose

Antiseptic, Hand Sanitizer

Use

Hand Sanitizer to help reduce bacteria that potentially can cause disease. For use when soap and water are not available.

Warnings

Flammable, keep away from fire or flame.

For external use only.

Do not use

- on open wounds

When using this product keep out of eyes, ears, and mouth. In case of contact with eyes, rinse eyes thoroughly with water.
Stop use and ask a doctor if irritation or rash occurs. These may be signs of a serious condition.
Keep out of reach of children. If swallowed, get medical help or contact a Poison Control Center right away.

Stop use and ask a doctor if irritation or rash occurs. These may be signs of a serious condition.

Keep out of reach of children. If swallowed, get medical help or contact a Poison Control Center right away.

Directions

- Place enough product on hands to cover all surfaces. Rub hands together until dry.
- Supervise children under 6 years of age when using this product to avoid swallowing.

Other information

- Store between 15-30C (59-86F)
- Avoid freezing and excessive heat above 40C (104F)

Inactive ingredients

Purified water USP, glycerin, carbomer, triethanolamine.

Package Label - Principal Display Panel

200000 mL NDC: 77143-005-01

3785 mL NDC: 77143-005-02

1000 mL NDC: 77143-005-03

500 mL NDC: 77143-005-04

19000 mL NDC: 77143-005-05

118 mL NDC: 77143-005-06

250 mL NDC: 77143-005-07

350 mL NDC: 77143-005-09